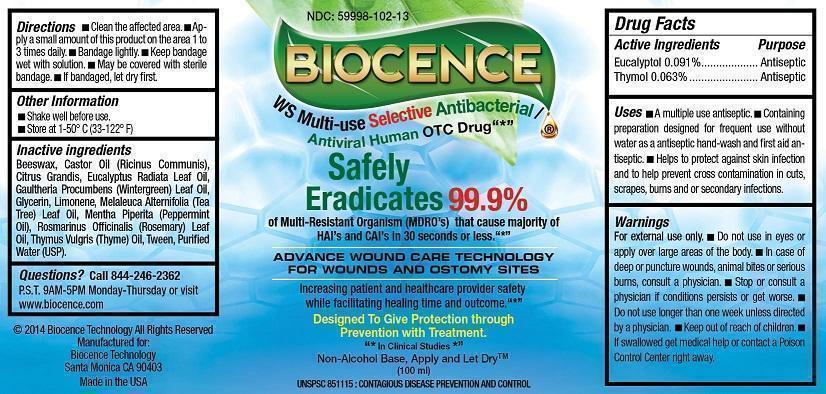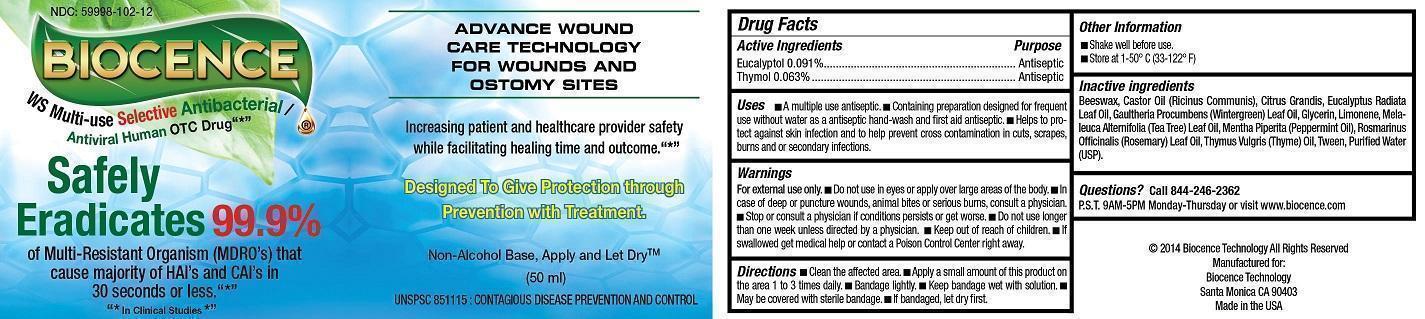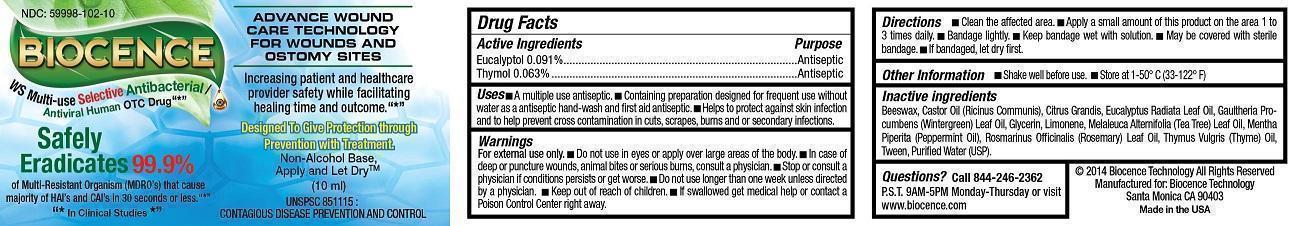 DRUG LABEL: BIOCENCE
NDC: 59998-202 | Form: SPRAY
Manufacturer: Bio-Germ Protection LLC
Category: homeopathic | Type: HUMAN OTC DRUG LABEL
Date: 20251210

ACTIVE INGREDIENTS: EUCALYPTOL 0.091 g/100 mL; THYMOL 0.063 g/100 mL
INACTIVE INGREDIENTS: YELLOW WAX; CASTOR OIL; GRAPEFRUIT; EUCALYPTUS GLOBULUS LEAF; GLYCERIN; LIMONENE, (+)-; PEPPERMINT OIL; ROSEMARY OIL; TEA TREE OIL; THYME OIL; WATER; POLYSORBATE 20; METHYL SALICYLATE

BIOCENCE (as PLD) - LIQUID (59998-202)

ACTIVE INGREDIENTS

EUCALYPTOL 0.091%

THYMOL 0.063%

PURPOSE

ANTISEPTIC

USES

- A MULTIPLE USE ANTISEPTIC
- CONTAINING PREPARATION DESIGNED FOR FREQUENT USE WITHOUT WATER AS AN ANTISEPTIC HANDWASH AND FIRST AID ANTISEPTIC.
- HELPS TO PROTECT AGAINST SKIN INFECTION AND TO HELP PREVENT CROSS CONTAMINATION IN CUTS, SCRAPES, BURNS, AND OR SECONDARY INFECTIONS.

WARNINGS

FOR EXTERNAL USE ONLY.

- DO NOT USE IN EYES OR APPLY OVER LARGE AREAS OF THE BODY.
- IN CASE OF DEEP OR PUNCTURE WOUNDS, ANIMAL BITES, OR SERIOUS BURNS, CONSULT A PHYSICIAN.
- STOP OR CONSULT A PHYSICIAN IF CONDITIONS PERSIST OR GET WORSE.
- DO NOT USE LONGER THAN ONE WEEK UNLESS DIRECTED BY A PHYSICIAN.

- KEEP OUT OF REACH OF CHILDREN.
- IF SWALLOWED GET MEDICAL HELP OR CONTACT A POISON CONTROL CENTER RIGHT AWAY.

DIRECTIONS

- CLEAN THE AFFECTED AREA.
- APPLY A SMALL AMOUNT OF THIS PRODUCT ON THE AREA 1 TO 3 TIMES DAILY.
- BANDAGE LIGHTLY.
- KEEP BANDAGE WET WITH SOLUTION.
- SPRAY A SMALL AMOUNT OF THIS PRODUCT ON THE AREA 1 TO 3 TIMES DAILY.
- MAY BE COVERED WITH STERILE BANDAGE.
- IF BANDAGED, LET DRY FIRST.

OTHER INFORMATION

- SHAKE WELL BEFORE USE.
- STORE AT 1-50°C (33-122°F)

INACTIVE INGREDIENTS

BEESWAX, CASTOR OIL (RICINUS COMMUNIS), CITRUS GRANDIS, EUCALYPTUS RADIATA LEAF OIL, GAULTHERIA PROCUMBENS (WINTERGREEN) LEAF OIL, GLYCERIN, LIMONENE, MELALEUCA ALTERNIFOLIA (TEA TREE) LEAF OIL, MENTHA PIPERITA (PEPPERMINT) OIL, ROSMARINUS OFFICINALIS (ROSEMARY) LEAF EXTRACT, THYMUS VULGARIS (THYME) OIL, TWEEN, WATER (AQUA).

QUESTIONS?

CALL (844) BIOCENCE/ (844) 246-2362 P.S.T. 9AM - 5PM MONDAY-THURSDAY OR VISIT WWW.BIOCENCE.COM